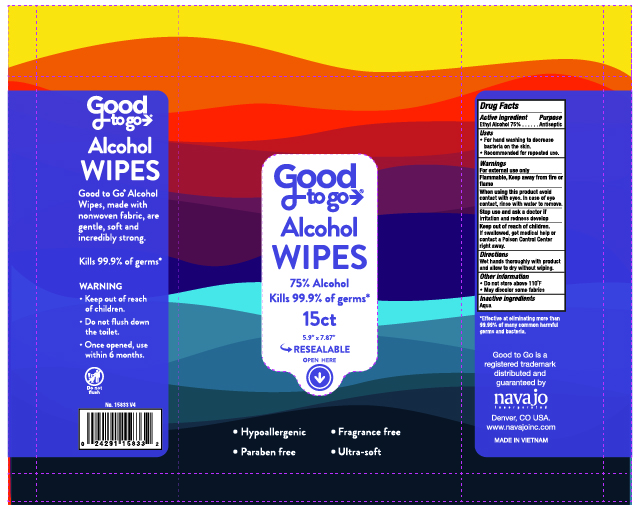 DRUG LABEL: Good to Go Alcohol Wipes 15ct
NDC: 67751-238 | Form: SWAB
Manufacturer: Navajo Manufacturing Company Inc.
Category: otc | Type: HUMAN OTC DRUG LABEL
Date: 20250825

ACTIVE INGREDIENTS: ALCOHOL 75 g/100 g
INACTIVE INGREDIENTS: WATER

Good to Go Alcohol Wipes 15ct

Active ingredient

Ethyl Alcohol 75%

Purpose

Antiseptic

Uses

■ For hand washing to decrease bacteria on the skin. Recommended for repeated use.

Warnings

For external use only
Flammable. Keep away from fire or flame.

When using this product avoid contact with eyes. In case of eye contact, rinse with water to remove.

Stop use and ask a doctor if irritation and redness develop.

Keep out of reach of children. If swallowed, get medical help or contact a Poison Control Center right away.

Directions

■Wet hands thoroughly wi th product and allow to
dry without wiping.

Inactive Ingredients

Aqua

Principal Display Panel

Navajo Incorporated

Denver, CO USA

www.navajoinc.com

Made in Vietnam